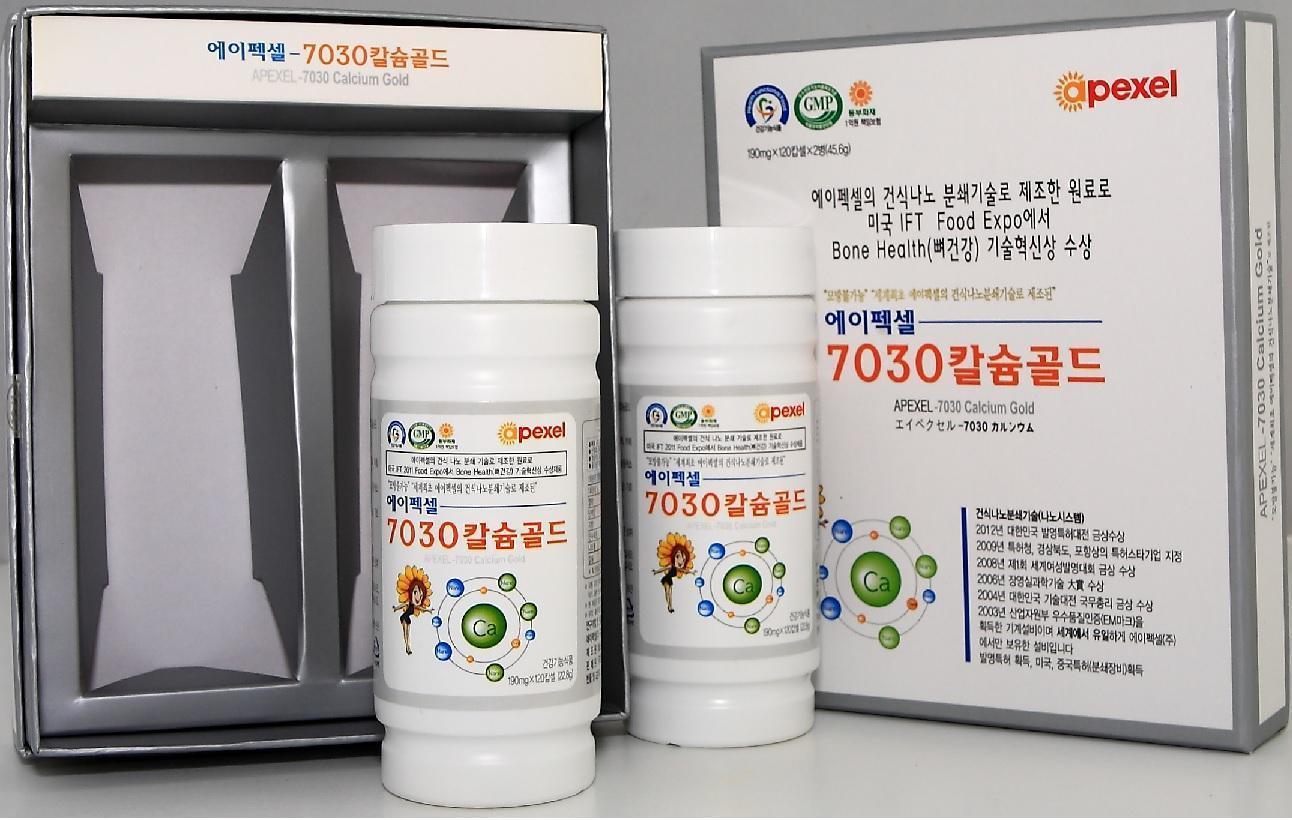 DRUG LABEL: 7030 Calcium Gold
NDC: 55259-0001 | Form: CAPSULE
Manufacturer: Apexel Co., Ltd
Category: otc | Type: HUMAN OTC DRUG LABEL
Date: 20240220

ACTIVE INGREDIENTS: CALCIUM 0.99 mg/1 1
INACTIVE INGREDIENTS: MAGNESIUM; ZINC OXIDE; SELENIUM; GERMANIUM; IRON; POTASSIUM; MANGANESE

Drug Facts

ACTIVE INGREDIENT

calcium

INACTIVE INGREDIENT

magnesium, zinc oxide, selenium, germanium, iron, potassium, manganese

PURPOSE

- to prevent and cure the osteoporosis
- to prevent and cure the disease of cardiac and vascular
- to promote growth and healing

keep out of reach of the children

INDICATIONS AND USAGE

take two tablets everty time, two times a day with enough water

• Do not use during pregnant, breast-feeding, or menstrual cycle
• Keep this product out of reach of children under 3 years old

DOSAGE AND ADMINISTRATION

for oral use only